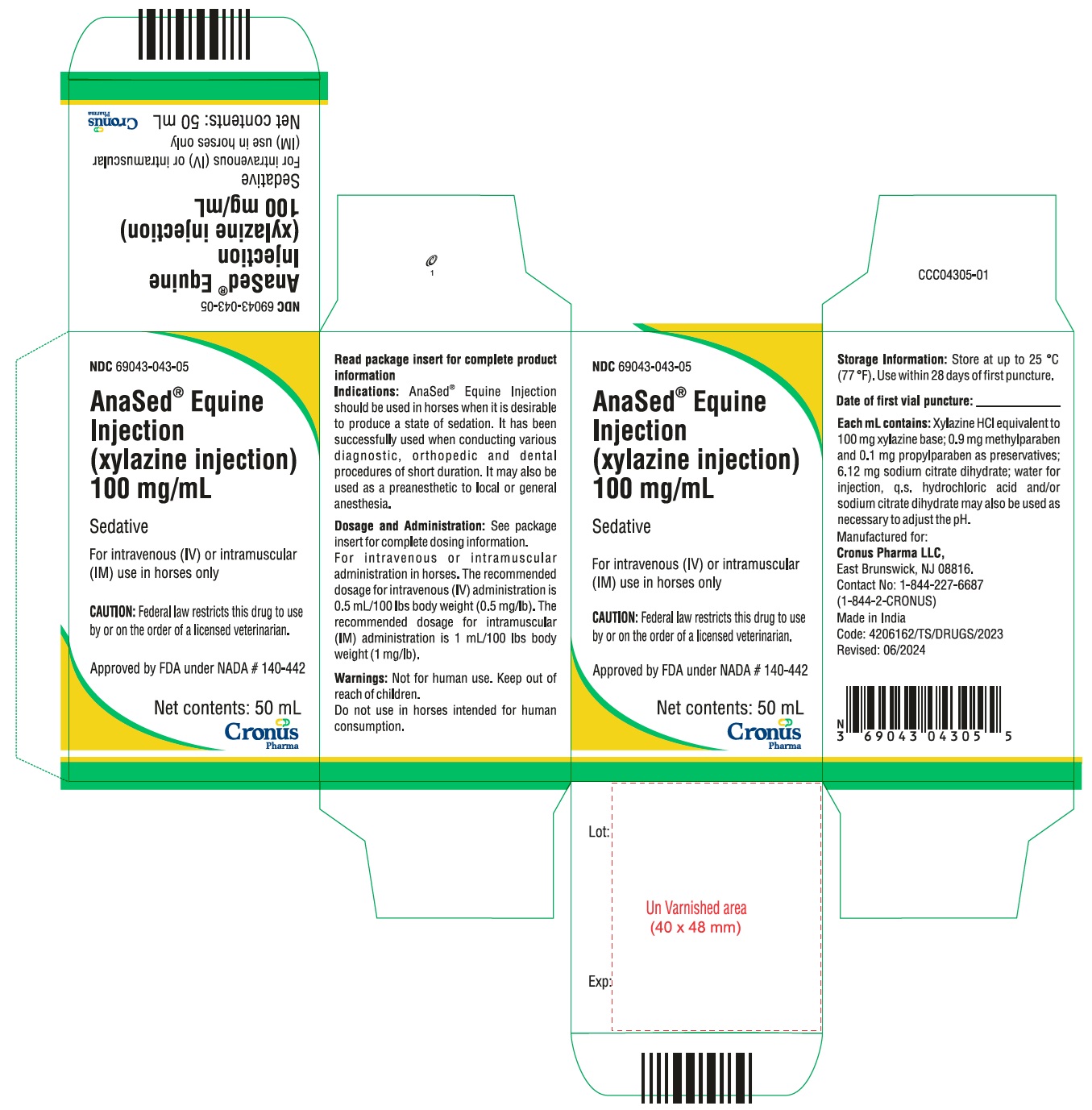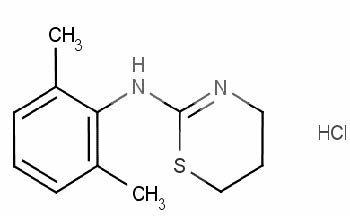 DRUG LABEL: Anased
NDC: 69043-043 | Form: INJECTION, SOLUTION
Manufacturer: Cronus Pharma LLC
Category: animal | Type: PRESCRIPTION ANIMAL DRUG LABEL
Date: 20250110

ACTIVE INGREDIENTS: XYLAZINE HYDROCHLORIDE 100 mg/1 mL

Anased Equine Injection
(xylazine injection)
100 mg/mL

For intravenous (IV) or intramuscular (IM) use in horses only

CAUTION: Federal law restricts this drug to use by or on the order of a licensed veterinarian.

Sedative

DESCRIPTION:

Xylazine is an alpha2-adrenoreceptor agonist with sedative properties. The chemical name for Xylazine is 2-(2,6-dimethylphenylamino)-4H-5,6-dihydro-1,3-thiazine. The formula for the hydrochloride salt is C12H16N2S.HCl. Anased® Equine Injection (xylazine injection) is a clear, colorless solution. Each mL of sterile Anased® Equine Injection contains xylazine HCl equivalent to 100 mg xylazine base; 0.9 mg methylparaben and 0.1 mg propylparaben as preservatives; 6.12 mg sodium citrate dihydrate; water for injection, q.s. hydrochloric acid and/or sodium citrate dihydrate may also be used as necessary to adjust the pH.

INDICATIONS AND USAGE

INDICATIONS: Anased® Equine Injection should be used in horses when it is desirable to produce a state of sedation. It has been successfully used when conducting various diagnostic, orthopedic and dental procedures of short duration. It may also be used as a preanesthetic to local or general anesthesia.

DOSAGE AND ADMINISTRATION: For intravenous or intramuscular administration in horses. The recommended dosage for intravenous (IV) administration is 0.5 mL/100 lbs body weight (0.5 mg/lb). The recommended dosage for intramuscular (IM) administration is 1 mL/100lbs body weight (1 mg/lb).

Following the administration of Anased® Equine Injection the horse should be allowed to rest quietly until the full effect has been reached. These dosages produce a state of sedation which is usually maintained for 1 to 2 hours (See Clinical Pharmacology).

Preanesthetic to local anesthesia: At the recommended dosages Anased® Equine Injection may be used in conjunction with local anesthetics, such as procaine and lidocaine.

Preanesthetic to general anesthesia: At the recommended dosages Anased® Equine Injection produces an additive effect to central nervous system depressants, such as sodium pentobarbital, sodium thiopental and sodium thiamylal. Accordingly, the dosage of such products should be reduced and administered to the desired effect. Generally, 1/3 to 1/2 of the calculated dosage of the barbiturates will be needed to produce a surgical plane of anesthesia. Postanesthetic or emergence excitement has not been observed in horses preanesthetized with Anased® Equine Injection.

Anased® Equine Injection has been successfully used as a preanesthetic agent for sodium pentobarbital, sodium thiopental, sodium thiamylal, nitrous oxide, ether, halothane, guaifenesin and methoxyflurane anesthesia.

CONTRAINDICATIONS

CONTRAINDICATIONS: Anased® Equine Injection should not be used in conjunction with neuroleptics or tranquilizers.

WARNINGS: User Safety Warnings

Not for use in humans. Keep out of reach of children.

Avoid skin, eye or mucosal contact. Use caution while handling and using filled syringes.

Absorption of the active ingredients is possible following exposure via the skin, eye or mucosa. In case of accidental eye exposure, flush eyes with water for 15 minutes, remove contact lenses then continue to flush. In case of accidental skin exposure, wash with soap and water and remove contaminated clothing. If symptoms occur, seek the advice of a physician.

In case of accidental oral intake or self-injection, seek medical advice immediately and show the package insert to the physician. DO NOT DRIVE as sedation, loss of consciousness, and changes in blood pressure may occur.

Persons with cardiovascular disease (for example, hypertension or ischemic heart disease) should take special precautions to avoid any exposure to this product.

Pregnant women should exercise special caution to avoid exposure. Uterine contractions and decreased fetal blood pressure may occur after accidental systemic exposure.

Persons with known hypersensitivity to any of the ingredients should avoid contact with Anased® Equine Injection.

Caution should be exercised when handling sedated animals. Handling or any other sudden stimuli, including noise, may cause a defense reaction in an animal that appears to be heavily sedated.

Note to physician: Anased® Equine Injection contains xylazine HCl, an alpha2-adrenoceptor agonist. Symptoms after absorption or accidental self-injection may include dose-dependent sedation, respiratory depression, bradycardia, tachycardia, and hypotension.

Animal Safety Warnings

Intracarotid arterial injection should be avoided. As with many drugs, including tranquilizers, immediate and violent seizures followed by collapse may result from inadvertent administration into the carotid artery. Although the reaction with Anased® Equine Injection is usually transient and the recovery rapid and complete, special care should be taken to assure that the needle is in the jugular vein rather than the carotid artery.

Other Warnings

Do not use in horses intended for human consumption.

PRECAUTIONS:

Debilitated horses with depressed respiration, cardiac disease, renal or liver impairment, shock or any other stress conditions should be carefully monitored whenever Anased® Equine Injection is administered.

Anased® Equine Injection produces an additive effect to central nervous system depressants and caution should be taken when administering barbiturate compounds in conjunction with Anased® Equine Injection. Barbiturates should be administered at a reduced dosage and to the desired effect, and when injected intravenously should be given slowly.

Arrhythmias resulting in partial atrioventricular (AV) blocks and bradycardia are transient changes which may occur, but that can be counteracted to a large degree by the administration of atropine prior to or following Anased® Equine Injection (xylazine injection).

Analgesic effect is variable and depth should be carefully determined prior to surgical or clinical procedures. Variability of analgesia occurs most frequently at the distal extremities of horses. In spite of sedation, the practitioner should proceed with caution since defense reactions may not be diminished.

Horses under the influence of Anased® Equine Injection are particularly sensitive to noise and care should be taken accordingly to avoid risk of injury. Sedation for transport is most successful if actual transport is initiated after full effect of the drug has been obtained and the horse’s stability maintained in the standing position.

ADVERSE REACTIONS

ADVERSE REACTIONS: The deep sedation produced by Anased® Equine Injection is characterized by lowering of the head, drooping of the eyelids and lower lip and a marked reluctance to move. Most horses given Anased® Equine Injection sweat around the ears and poll region and may seem particularly sensitive to sharp auditory stimuli during the recovery period. The respiratory and pulse rate are reduced as in natural sleep. Transient changes in the conductivity of the cardiac muscle (resulting in partial AV blocks), bradycardia, decreased cardiac output and a rise in arterial blood pressure may occur following intravenous administration.

CONTACT INFORMATION: To report suspected adverse reactions, for technical assistance, or to obtain a copy of the Safety Data Sheet (SDS), call Cronus Pharma at (844) 227-6687. For additional information about adverse drug experience reporting for animal drugs, contact FDA at 1-888-FDA-VETS or www.fda.gov/reportanimalae

CLINICAL PHARMACOLOGY

CLINICAL PHARMACOLOGY: Xylazine Injection is pharmacologically classified as a non-narcotic sedative. The drug causes sedation by acting upon alpha-adrenergic receptors in the brain to prevent the release of norepinephrine. Xylazine Injection also produces muscle relaxation by inhibiting the intraneural transmission of impulses in the central nervous system.

Deep sedation develops in the horse within 10 to 15 minutes after intramuscular injection, and within 3 to 5 minutes following intravenous administration.

Deep sedation lasts 15 to 20 minutes, while a sleep-like state, the depth of which is dose-dependent, is usually maintained for 1 to 2 hours following intramuscular administration of the drug at the recommended dosage. Recovery is complete with 30-40 minutes following intravenous injection.

In animals under the influence of Xylazine Injection, the respiratory and pulse rates are reduced as in a natural sleep. The intramuscular injection of Xylazine produces only negligible effects on the cardiovascular and respiratory systems. However, intravenous administration in the horse may cause transient changes in the conductivity of the cardiac muscle, evidenced by partial AV blocks, bradycardia, decreased cardiac output and a rise in arterial blood pressure. These actions are transient and can be counteracted to a large degree by the administration of atropine prior to or following Xylazine Injection. Xylazine Injection has no effect on blood clotting time or other hematologic parameters.

TARGET ANIMAL SAFETY: Xylazine Injection is tolerated in horses at 10 times the recommended dosage, however doses of this magnitude produce muscle tremors and long periods of sedation.

HOW SUPPLIED

HOW SUPPLIED: Anased® Equine Injection, 100 mg/mL, is available in 50 mL multiple-dose vials.

STORAGE AND HANDLING

STORAGE: Store at up to 25 °C (77 °F). Use within 28 days of first puncture.

Approved by FDA under NADA # 140-442

Manufactured for:
Cronus Pharma LLC
East Brunswick, NJ 08816

Contact No: 1-844-227-6687
(1-844-2-CRONUS)

4206162/TS/DRUGS/2023

Made in India

Revised: 09/2024

PACKAGE LABEL.PRINCIPAL DISPLAY PANEL

NDC 69043-043-05

Anased® Equine Injection

(Xylazine Injection)
100 mg/mL

Sedative

For intravenous (IV) or intramuscular (IM) use in horses only

CAUTION: Federal law restricts this drug to use by or on the order of a licensed veterinarian.

Approved by FDA under NADA # 140-442

Net contents: 50 mL